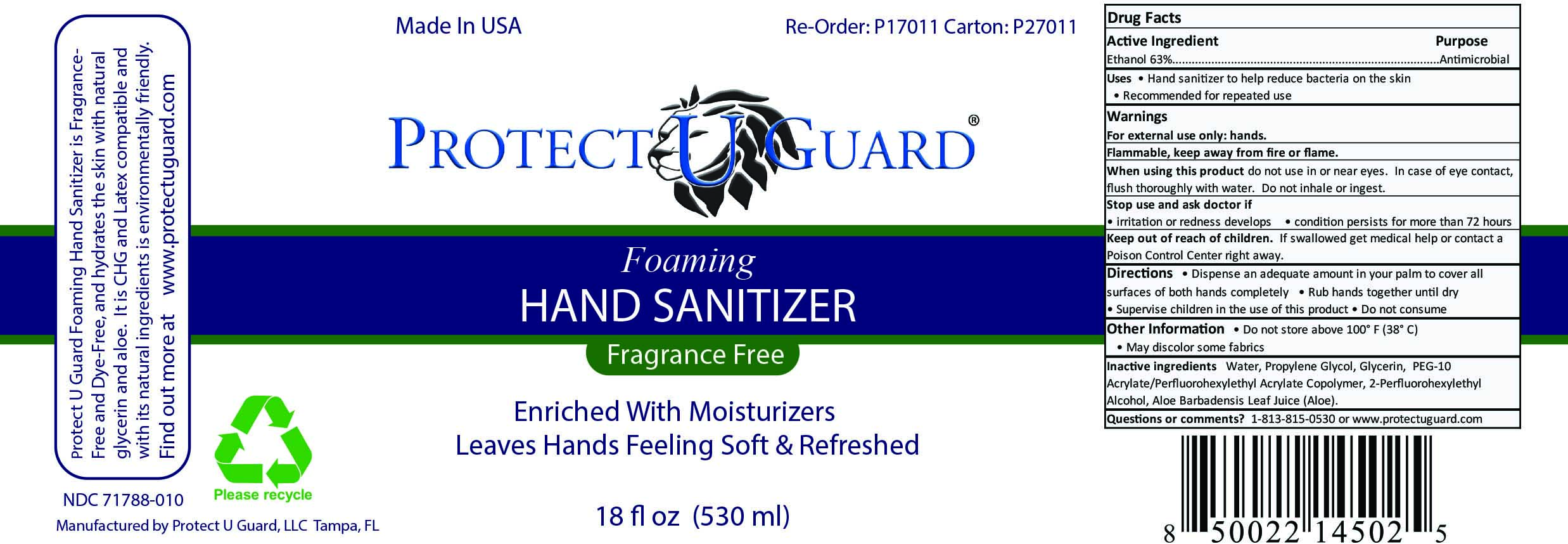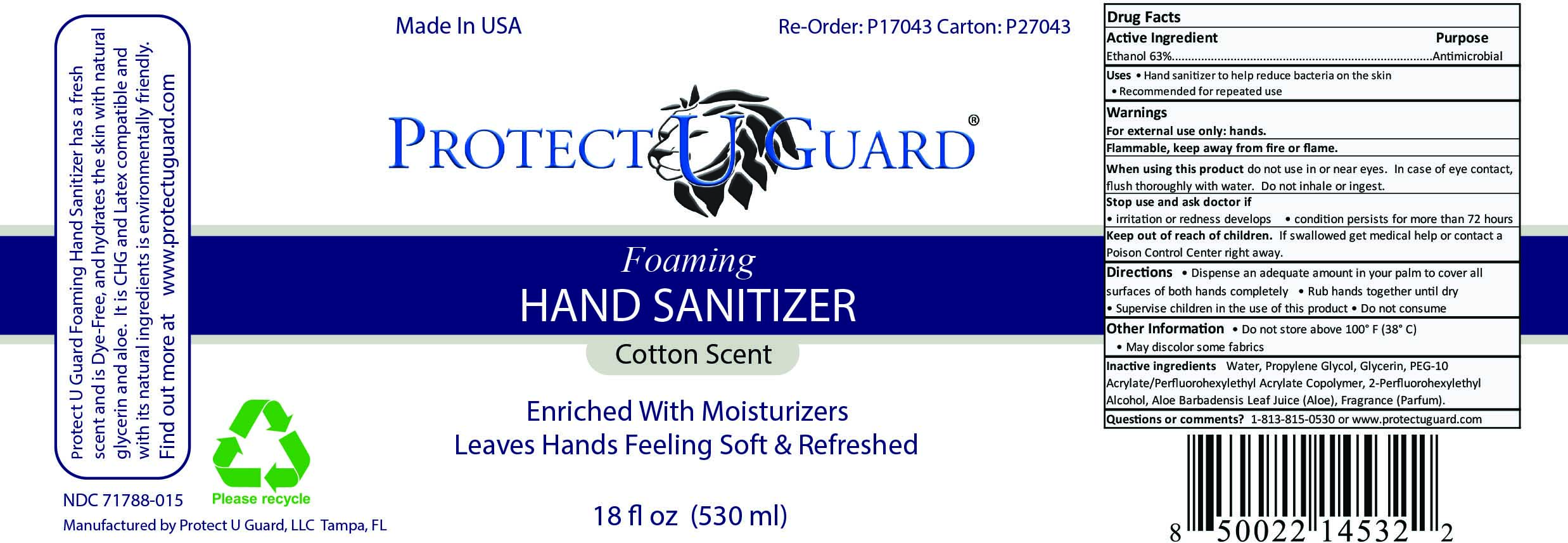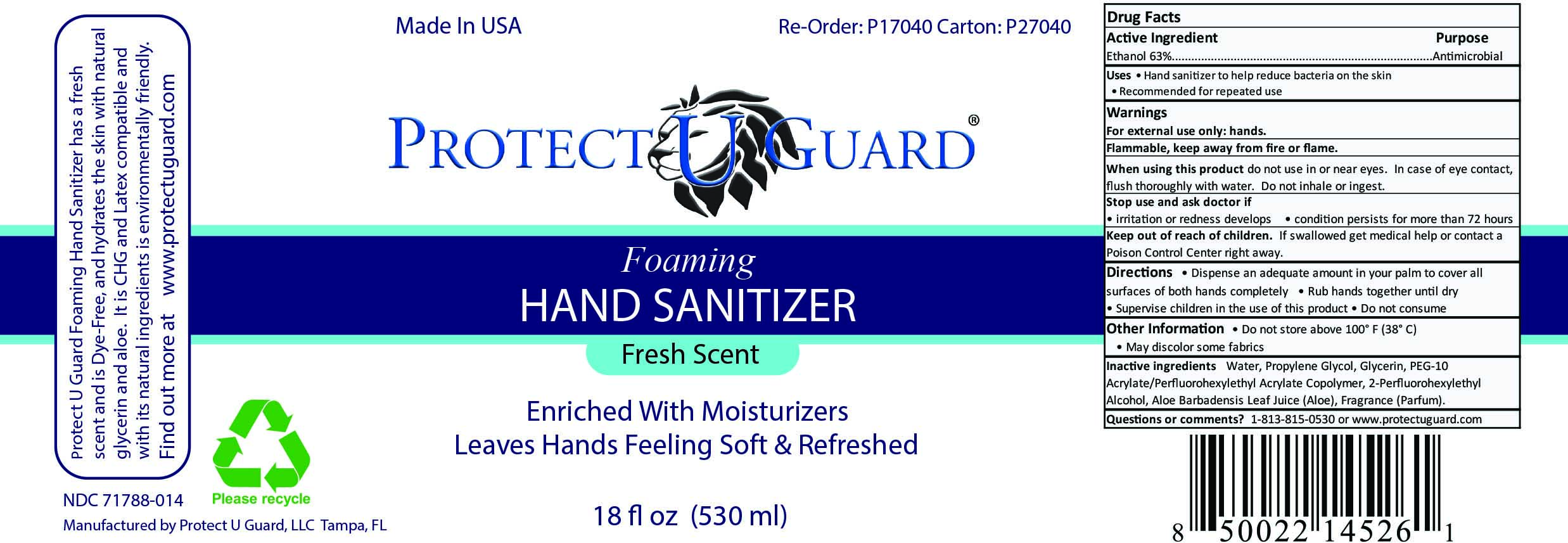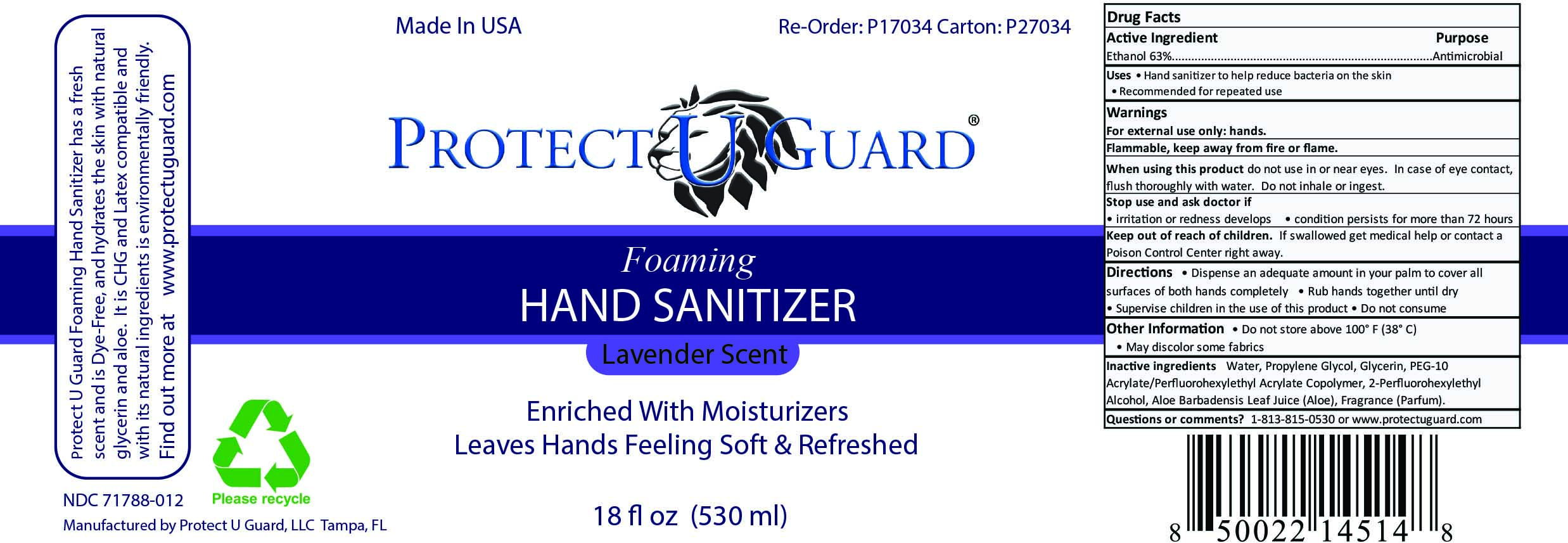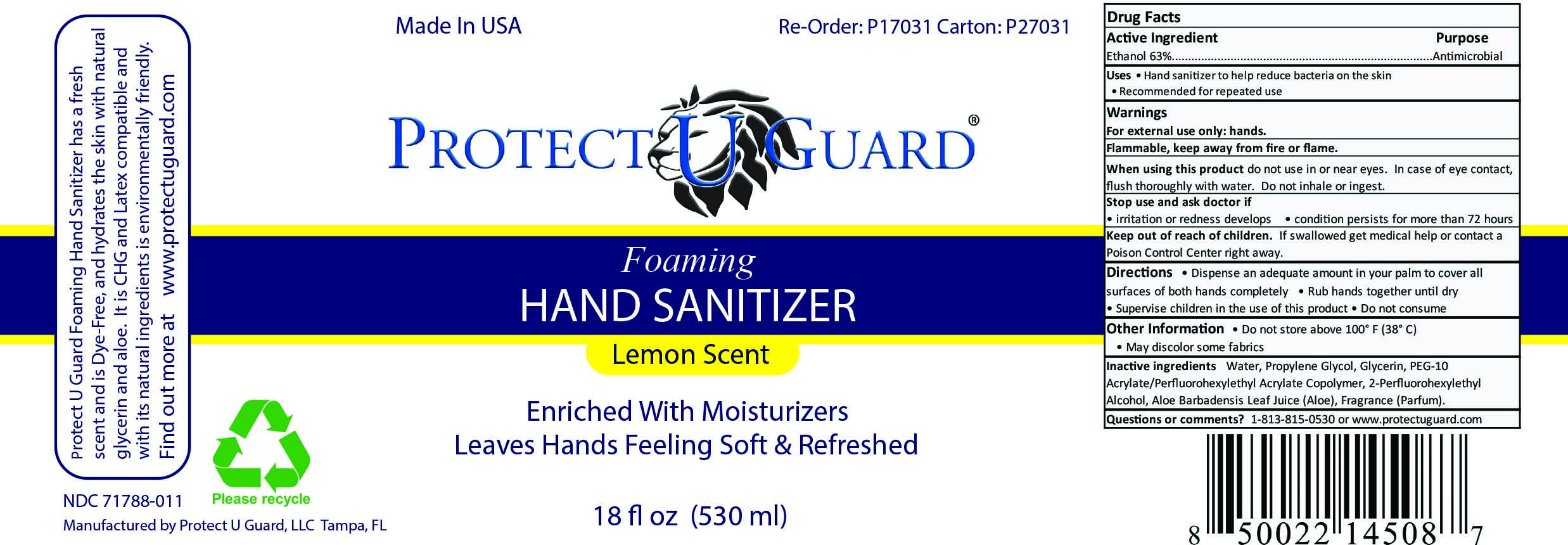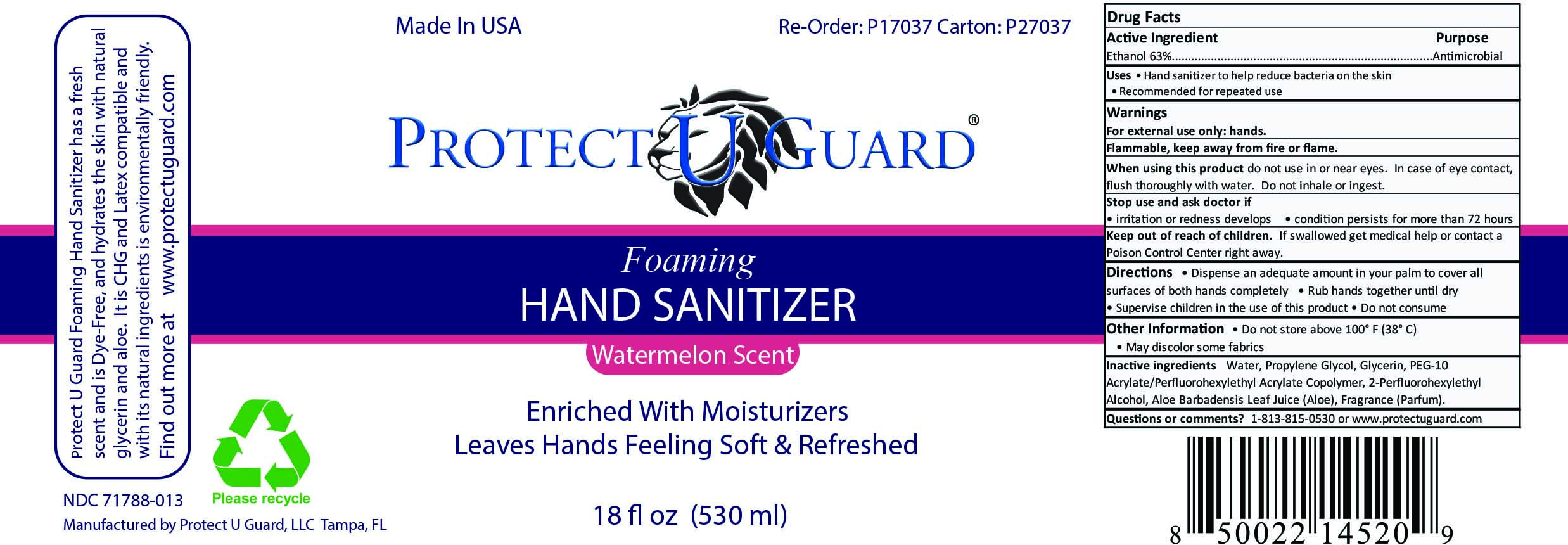 DRUG LABEL: Protect U Guard 63% Foaming Hand Sanitizer Lemon
NDC: 71788-011 | Form: LIQUID
Manufacturer: Protect U Guard, LLC
Category: otc | Type: HUMAN OTC DRUG LABEL
Date: 20241231

ACTIVE INGREDIENTS: ALCOHOL 63 mL/100 mL
INACTIVE INGREDIENTS: WATER; ALOE VERA LEAF; 2-(PERFLUOROHEXYL)ETHANOL; PEG-10 ACRYLATE/PERFLUOROHEXYLETHYL ACRYLATE COPOLYMER; PROPYLENE GLYCOL

Active Ingredient

Ethanol 63%

Purpose

Antimicrobial

Uses

Hand sanitizer to help reduce bacteria on the skin

Recommended for repeated use

Warnings

For External Use Only: hands.

Flammable, keep away from fire or flame.

When using this product do not use in or near eyes. In case of eye contact, flush thoroughly with water. Do not inhale or ingest.

Stop use and ask docotr if irritation and redness develops condition persists for more than 72 hours

Keep out of reach of children. If Swallowed, get medical help or contact a Poison Control Center right away.

Stop Use and Ask Doctor

if irritation and redness develop and persists for more than 72 hours.

Directions

Dispense an adequate amount in your palm to cover all surfaces of hands completely

Rub hands together until dry

Supervise children in the use of this product

Do not consume

Other Information

Do not store above 100o F (38o C)

May discolor some fabrics

Inactive Ingredients

Water, Propylene Glycol, Glycerin, PEG-10 Acrylate/Perfluorohexylethyl Acrylate Copolymer, 2-Perfluorohexylethyl Alcohol, Aloe Barbadensis Leaf Juice (Aloe), Fragrance (Parfum).

Questions or comments?

1-813-815-0530 or www.protectuguard.com